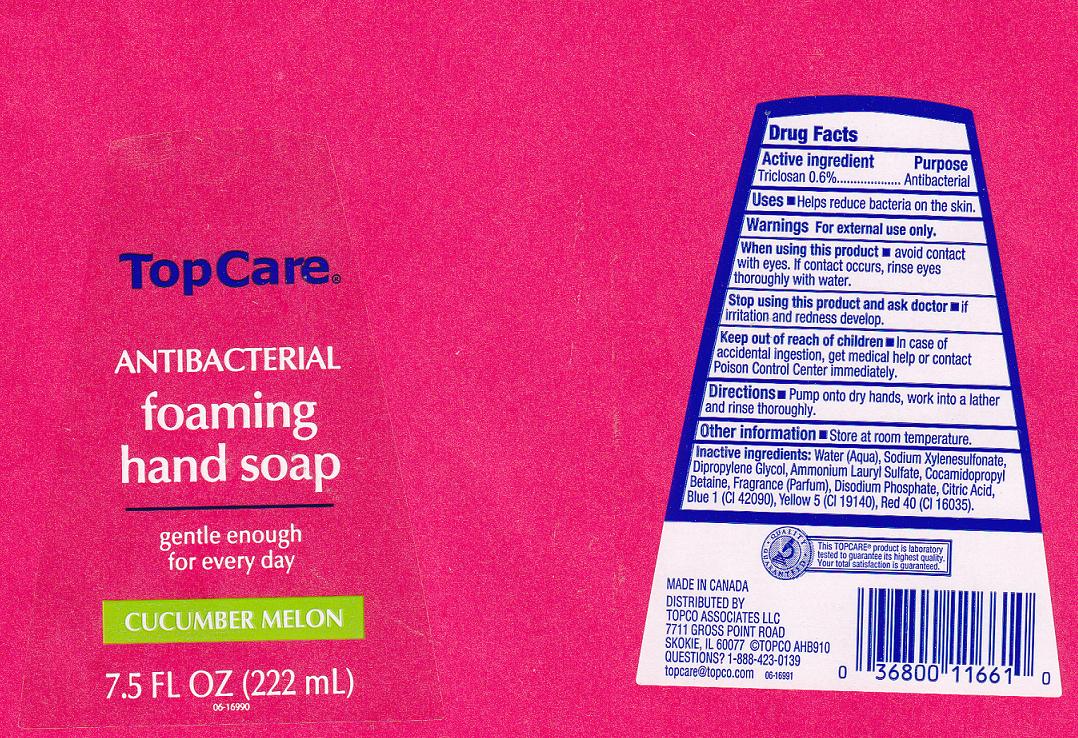 DRUG LABEL: Antibacterial Foaming
NDC: 36800-067 | Form: LIQUID
Manufacturer: Topco Associates llc
Category: otc | Type: HUMAN OTC DRUG LABEL
Date: 20110902

ACTIVE INGREDIENTS: TRICLOSAN 0.6 mL/100 mL
INACTIVE INGREDIENTS: WATER; SODIUM XYLENESULFONATE; DIPROPYLENE GLYCOL; AMMONIUM LAURYL SULFATE; COCAMIDOPROPYL BETAINE; SODIUM PHOSPHATE, DIBASIC; CITRIC ACID MONOHYDRATE; FD&C BLUE NO. 1; FD&C YELLOW NO. 5; FD&C RED NO. 40

Drug Facts Box - Back Label

Active Ingredient

Triclosan 0.6%

Purpose

Antibacterial

Uses

Helps reduce bacteria on the skin.

WARNINGS

For external use only.

When using this product

Avoid contact with eyes. If contact occurs, rinse eyes thoroughly with water.

Stop using this product and ask doctor if

if irritation and redness develop.

Keep out of reach of children

In case of accidental ingestion, get medical help or contact Poison Control Center immediately.

Directions

Pump onto dry hands, work into a lather and rinse thoroughly.

Other information

Enter section text here

Inactive ingredients

Water, Sodium Xylenesulfonate, Dipropylene Glycol, Ammonium Lauryl Sulfate, Cocamidopropyl Betaine, Fragrance, Disodium Phosphate, Citric Acid, Blue 1 (CI 42090), Yellow 5 (CI 19140), Red 40 (CI 16035).